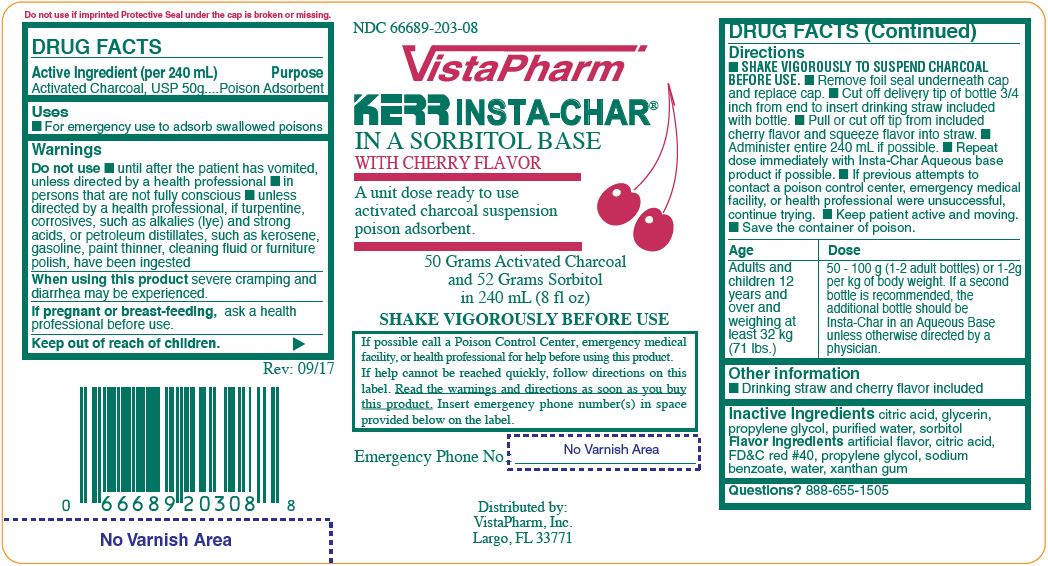 DRUG LABEL: INSTA-CHAR SORBITOL
NDC: 66689-203 | Form: SUSPENSION
Manufacturer: VistaPharm, LLC
Category: otc | Type: HUMAN OTC DRUG LABEL
Date: 20231120

ACTIVE INGREDIENTS: ACTIVATED CHARCOAL 50 g/240 mL
INACTIVE INGREDIENTS: ANHYDROUS CITRIC ACID; GLYCERIN; PROPYLENE GLYCOL; WATER; SORBITOL

INSTA-CHAR SORBITOL

Active Ingredient (per 240 mL)

Activated Charcoal, USP 50g

Purpose

Poison Adsorbent

Uses

- For emergency use to adsorb swallowed poisons.

Warnings

Do not use

- until after the patient has vomited, unless directed by a health professional
- in persons that are not fully conscious
- unless directed by a health professional, if turpentine, corrosives, such as alkalies (lye) and strong acids, or petroleum distillates, such as kerosene, gasoline, paint thinner, cleaning fluid or furniture polish, have been ingested

When using this product

severe cramping and diarrhea may be experienced.

If Pregnant or breast-feeding,

ask a health professional before use.

Directions

- Shake vigorously to suspend charcoal before use.
- Remove foil seal underneath cap and replace cap.
- Cut off delivery tip of bottle 3/4 inch from end to insert drinking straw included with bottle.
- Pull or cut off tip from included cherry flabor and squeeze flavor into straw.
- Administer entire 240 mL if possible.
- Repeat dose immediately with Insta-Char Aqueous base product if possible.
- If previous attempts to contact a poison control center. emergency medical facility, of health professionsl were unsuccessful, continue trying.
- Keep patient active and moving.
- Save the container of poison.

Age | Dose
Adults and children 12 and over and weighing at least 32 kg (71 lbs.) | 50-100 g (1-2 adult bottles) or 1-2g per kg of body weight. If a second bottle is recommended, the additional bottle should be Insta-Char in an Aqueous Base unless otherwise directed by a physician.

Other information

- Drinking straw and cherry flavor included

Inactive Ingredients

citric acid, glycerin, propylene glycol, purified water, sorbitol

Flavor Ingredients
artificial flavor, citric acid, FD and C red #40, propylene glycol, sodium benzoate, water, xanthan gum

Questions?

888-655-1505

BOXED WARNING

If possible call a Poison Control Center, emergency medical facility, or health professional for help before using this product. If help cannot be reached quickly, follow directions on this label. Read the warnings and directions as soon as you buy this product. Insert emergency phone number(s) in space provided below on the label.

Label

The product package shown above represents a sample of that currently in use. Additional packaging may also be available.

Inst-Char Sorbitol Poison adsorbent 240 mL

Distributed by:

VistaPharm, Inc.

Largo, FL 33771

Insta-Char Sorbitol 240 mL